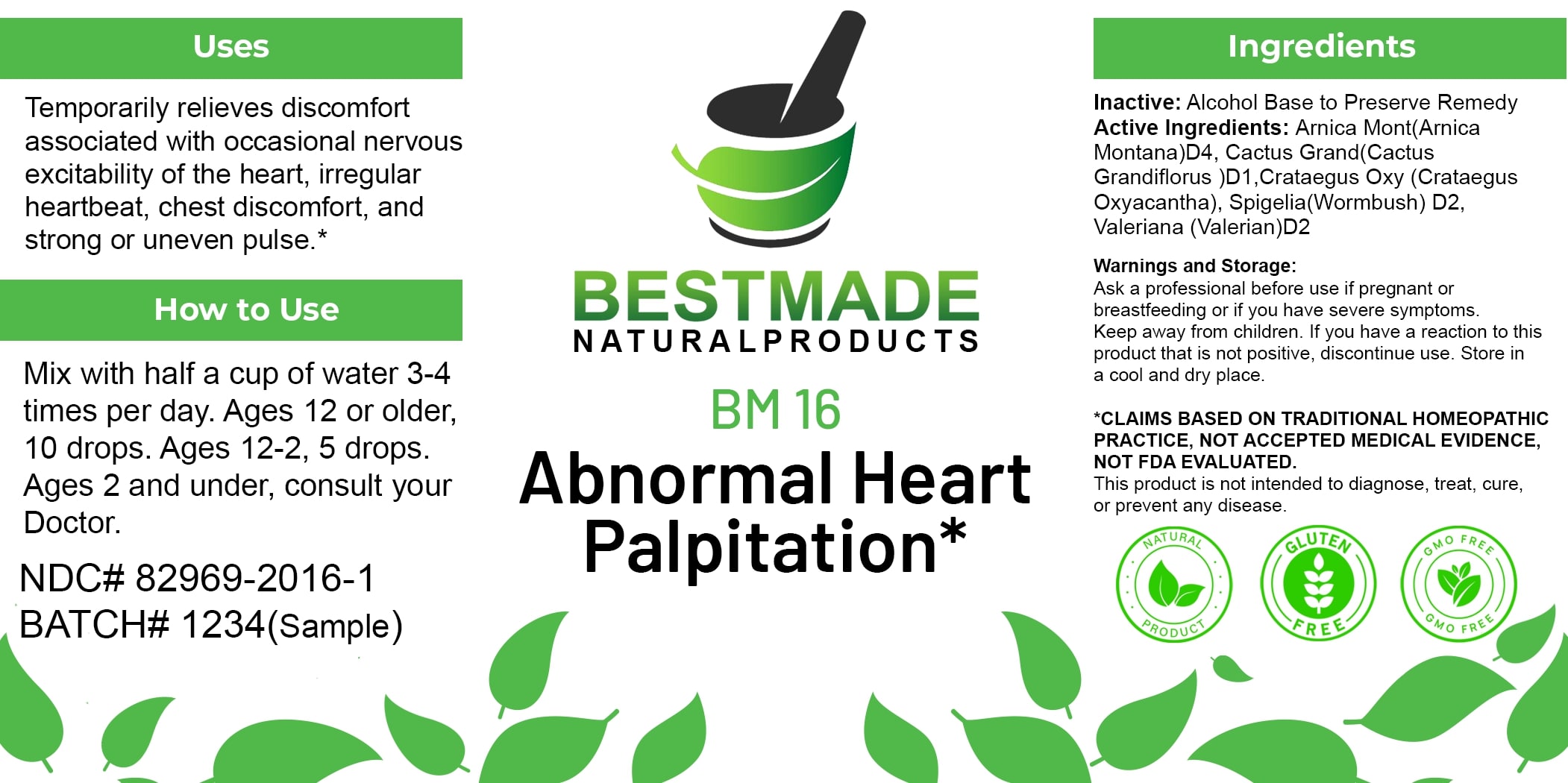 DRUG LABEL: Bestmade Natural Products BM16
NDC: 82969-2016 | Form: LIQUID
Manufacturer: Bestmade Natural Products
Category: homeopathic | Type: HUMAN OTC DRUG LABEL
Date: 20250122

ACTIVE INGREDIENTS: VALERIAN 30 [hp_C]/30 [hp_C]; HAWTHORN LEAF WITH FLOWER 30 [hp_C]/30 [hp_C]; ARNICA MONTANA 30 [hp_C]/30 [hp_C]; SELENICEREUS GRANDIFLORUS STEM 30 [hp_C]/30 [hp_C]; SPIGELIA ANTHELMIA 30 [hp_C]/30 [hp_C]
INACTIVE INGREDIENTS: ALCOHOL 30 [hp_C]/30 [hp_C]

BM16

INACTIVE INGREDIENT

Ingredients

Inactive: Alcohol Base to Preserve Remedy

DOSAGE AND ADMINISTRATION

How to Use

Mix with half a cup of water 3-4 times per day. Ages 12 or older, 10 drops. Ages 12-2, 5 drops. Ages 2 and under, consult your Doctor.

Uses

Temporarily relieves discomfort associated with occasional nervous excitability of the heart, irregular heartbeat, chest discomfort, and strong or uneven pulse.*

*CLAIMS BASED ON TRADITIONAL HOMEOPATHIC PRACTICE. NOT ACCEPTED MEDICAL EVIDENCE, NOT FDA EVALUATED.
This product is not intended to diagnose, treat, cure, or prevent any disease.

Active Ingredients:

Amica Mont(Amica Montana)D4, Cactus Grand(Cactus Grandiflorus)D1, Cratagus Oxy (Cratagus Oxyacantha), Spigella(Wormbush)D2, Valeriana (Valerian)D2

KEEP OUT OF REACH OF CHILDREN

Warnings and Storage:

Ask a professional before use if pregnant or breastfeeding or if you have severe symptoms. Keep away from children. If you have a reaction to this product that is not positive, discontinue use. Store in a cool and dry place.

Uses

Temporarily relieves discomfort associated with occasional nervous excitability of the heart, irregular heartbeat, chest discomfort, and strong or uneven pulse.*

*CLAIMS BASED ON TRADITIONAL HOMEOPATHIC PRACTICE. NOT ACCEPTED MEDICAL EVIDENCE, NOT FDA EVALUATED.
This product is not intended to diagnose, treat, cure, or prevent any disease.

Warnings and Storage:

Ask a professional before use if pregnant or breastfeeding or if you have severe symptoms. Keep away from children. If you have a reaction to this product that is not positive, discontinue use. Store in a cool and dry place.

*CLAIMS BASED ON TRADITIONAL HOMEOPATHIC PRACTICE. NOT ACCEPTED MEDICAL EVIDENCE, NOT FDA EVALUATED.
This product is not intended to diagnose, treat, cure, or prevent any disease.

Entire package label